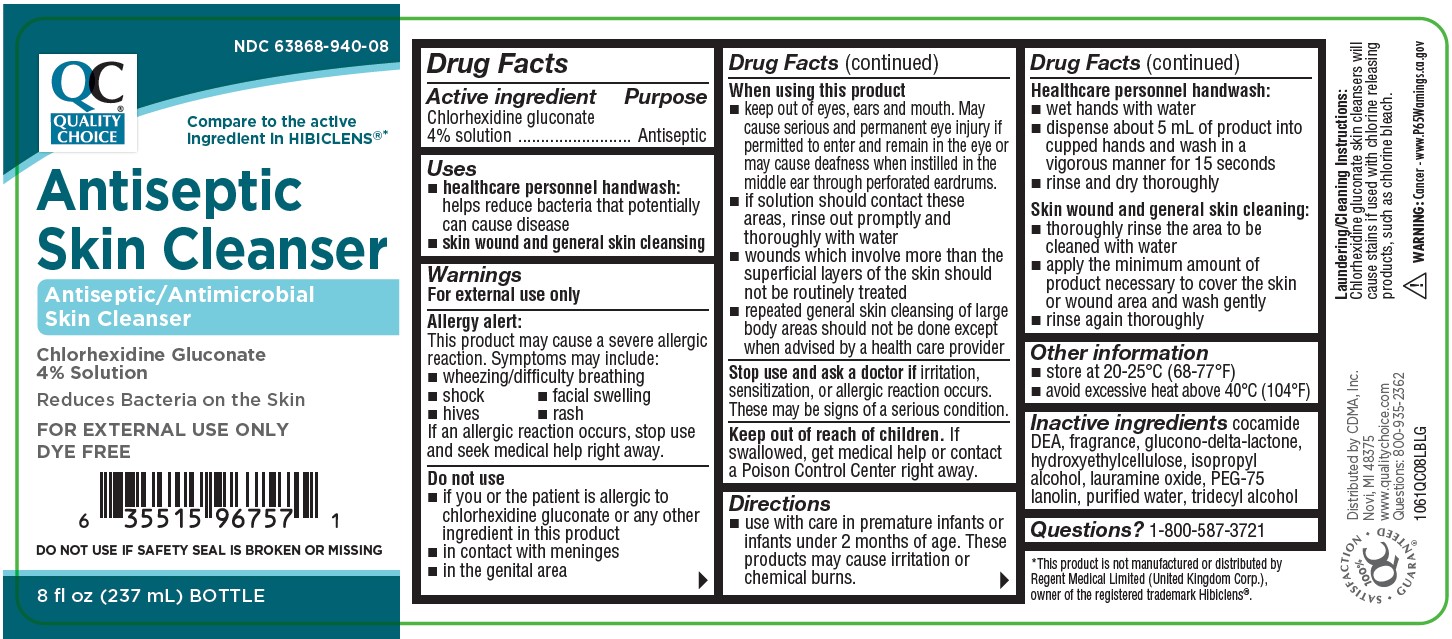 DRUG LABEL: Antiseptic Skin Cleanser
NDC: 63868-940 | Form: LIQUID
Manufacturer: Chain Drug Marketing Association Inc.
Category: otc | Type: HUMAN OTC DRUG LABEL
Date: 20251212

ACTIVE INGREDIENTS: CHLORHEXIDINE GLUCONATE 4 mg/100 mL
INACTIVE INGREDIENTS: LAURAMINE OXIDE; COCO DIETHANOLAMIDE; PEG-75 LANOLIN; HYDROXYETHYL CELLULOSE (2000 CPS AT 1%); ISOPROPYL ALCOHOL; WATER; TRIDECYL ALCOHOL; GLUCONOLACTONE

COMP Quality Choice 4% 8oz

Active Ingredients

Chlorhexidine gluconate 4% solution

Purpose

Antiseptic

Uses

- healthcare personnel handwash: helps reduce bacteria that potentially can cause disease
- skin wound and general skin cleansing

Warnings

For external use only

Allergy alert:

This product may cause a severe allergic reaction. Symptoms may include:

- wheezing/difficulty breathing
- shock
- facial swelling
- hives
- rash

If an allergic reaction occurs, stop use and seek medical help right away

Do not use

- if you or the patient is allergic to chlorhexidine gluconate or any other ingredient in this product
- in contact with meninges
- in the genital area

Keep out of reach of children.

If swallowed, get medical help or contact a Poison Control center right away

Stop use and ask doctor if

irritation, sensitization, or allergic reaction occurs. These may be signs of a serious condition.

When using this product

- keep out of eyes, ears, and mouth. May cause serious and permanent eye injury if permitted to enter and remain in the eye or may cause deafness when instilled in the middle ear through perforated eardrums.
- if solution should contact these areas, rinse out promptly and thoroughly with water
- wounds which involve more than the superficial layers of the skin should not be routinely treated
- repeated general skin cleansing of large body areas should not be done except when advised by a health care procider

Directions

- use with care in premature infants or infants under 2 months of age. These products may cause irritation or chemical burns.

Healthcare personnel handwash:

- wet hands with water
- dispense about 5ml of product into cupped hands and wash in a vigorous manner for about 15 seconds
- rinse and dry thoroughly

Skin wound and normal skin cleansing:

- thoroughly rinse the area to be cleaned with water
- apply the minimum amount of product necessary to cover the skin or wound area and wash gently
- rinse again thoroughly

Other information

- store at 20°-25° C (68°-77° F)
- avoid excessive heat above 40° C (104° F)

Inactive ingredients

cocamide DEA, fragrance, glucono-delta-lactone, hydroxyethylcellulose, isopropyl alcohol, lauramine oxide, PEG-75 lanolin, purified water, tridecyl alcohol.

Questions of comments?

1-800-587-3721

Other Information

DO NOT USE IF SAFETY SEAL IS BROKEN OR MISSING

Warning: This product contains a chemical (cocamide DEA) known to the State of California to cause cancer.

Laundering/Cleaning Instructions: Chlorhexidine gluconate skin cleansers will cause stains if used with chlorine releasing products. Rinse completely and use only non-chlorine detergents.

*This product is not manufactured or distributed by Mölnlycke Healthcare, owner of the registered trademark Hibiclens®.

OTHER SAFETY INFORMATION

Warning: Cancer - www.P65Warnings.gov

Laundering/Cleaning Instructions: Chlorhexidine gluconate skin cleansers will cause stains if used with chlorine releasing products, such as chlorine bleach.

*This product is not manufactured or distributed by Mölnlycke Healthcare, owner of the registered trademark Hibiclens®.

Package label and principal display panel

Quality Choice

NDC 63868-940-08

Compare to the active ingredient in HIBICLENS®*

Antiseptic Skin Cleanser

Antiseptic/Antimicrobial Skin Cleanser

Chlorhexidine Gluconate 4% Solution

Reduces Bacteria on the Skin

Net Contents: 8FL OZ (237 mL) BOTTLE

FOR EXTERNAL USE ONLY

DYE FREE

1061QC08LBLG